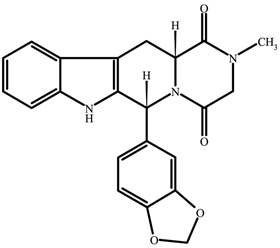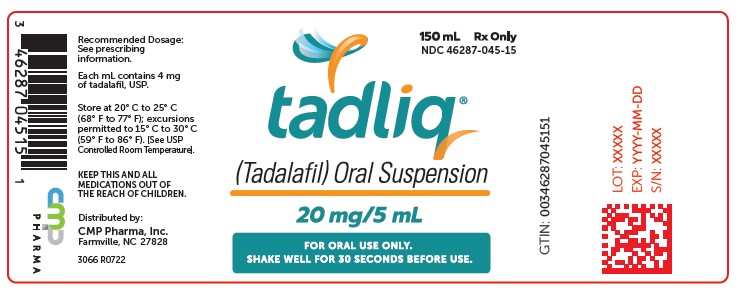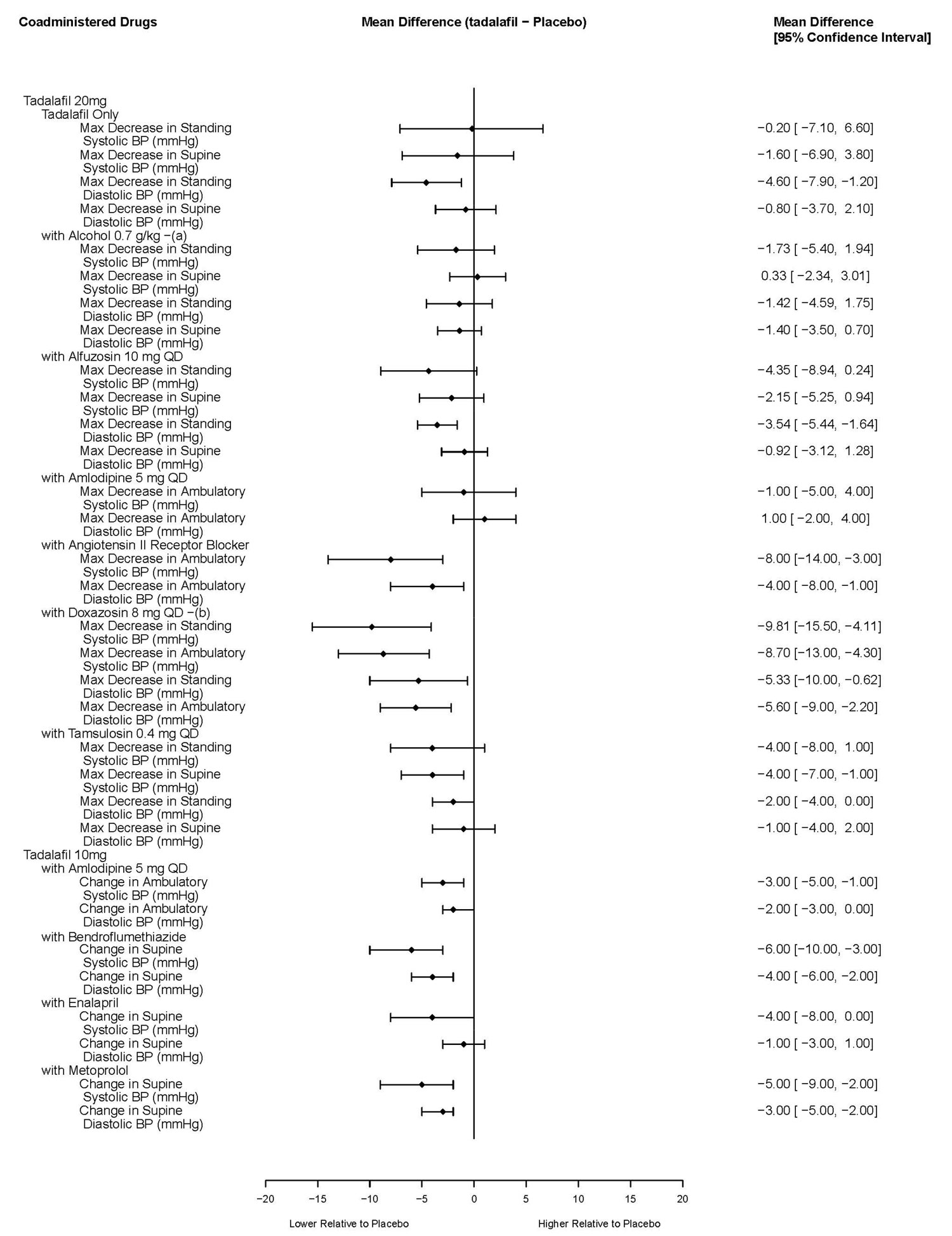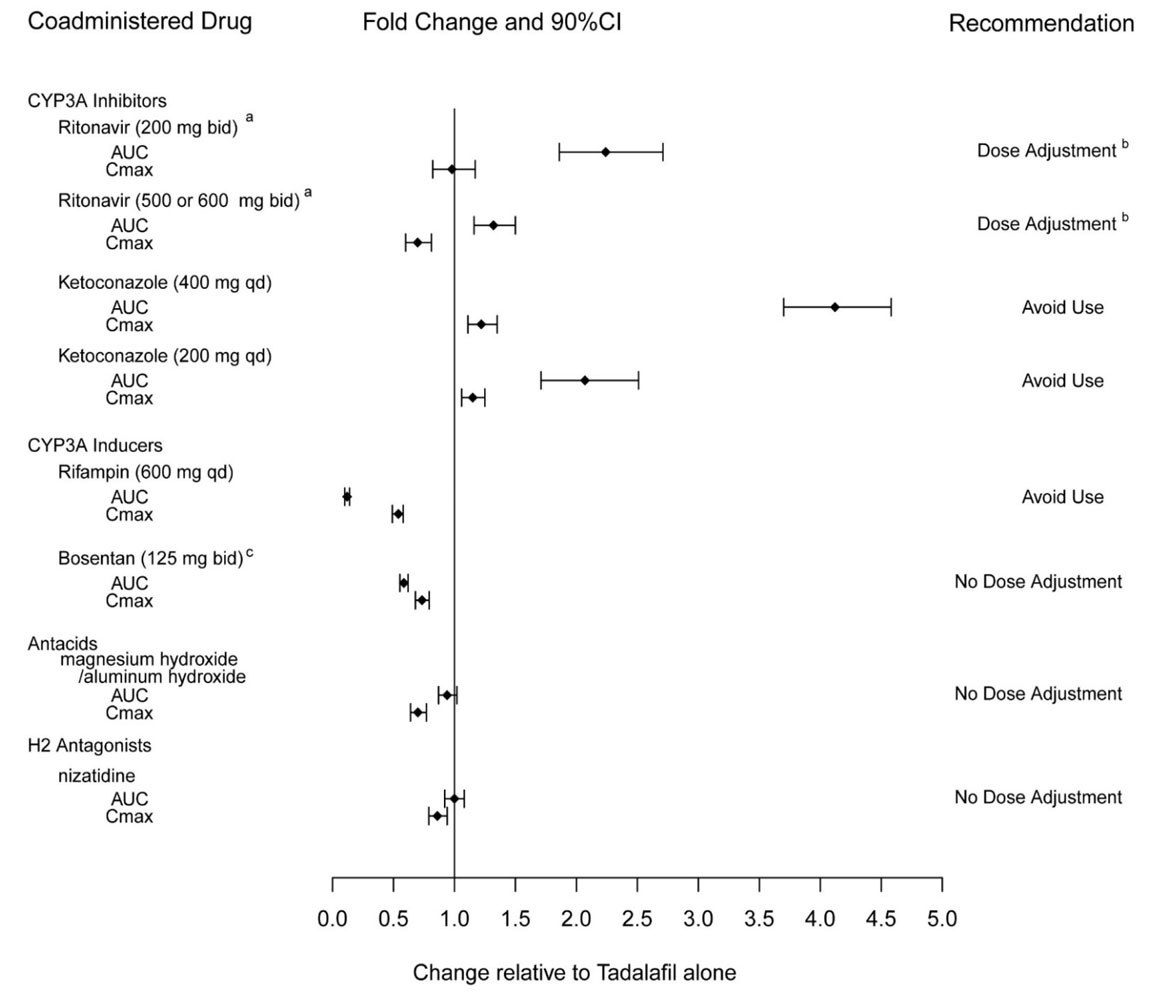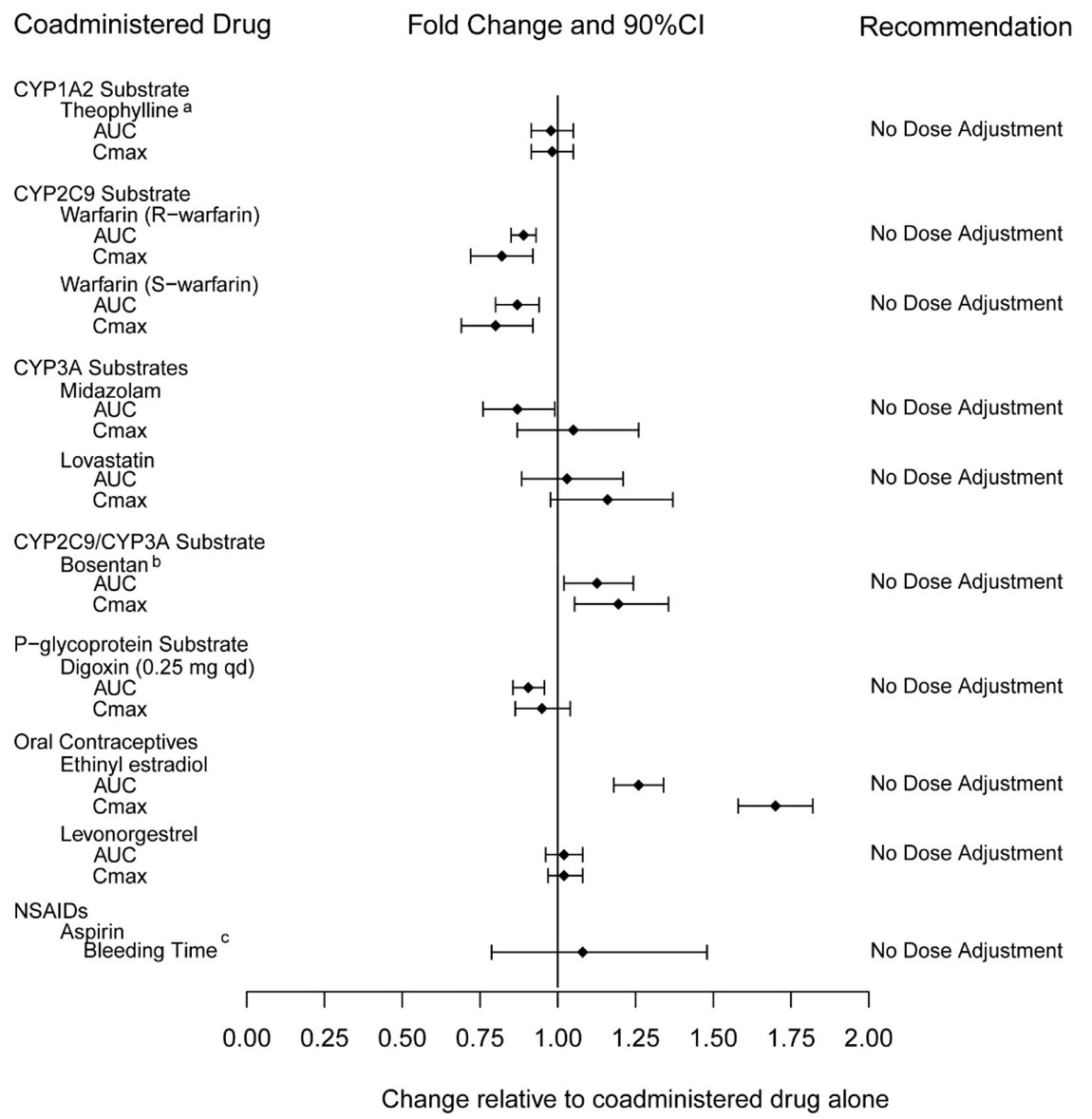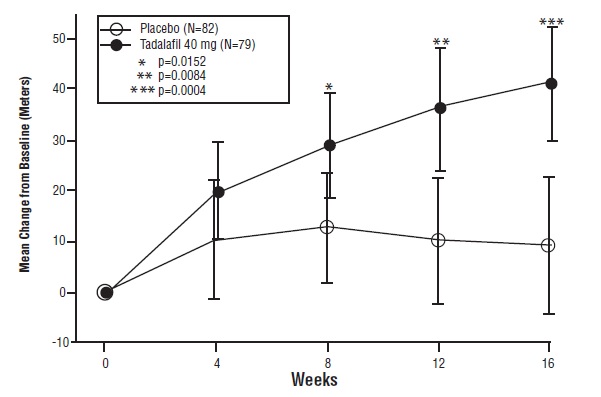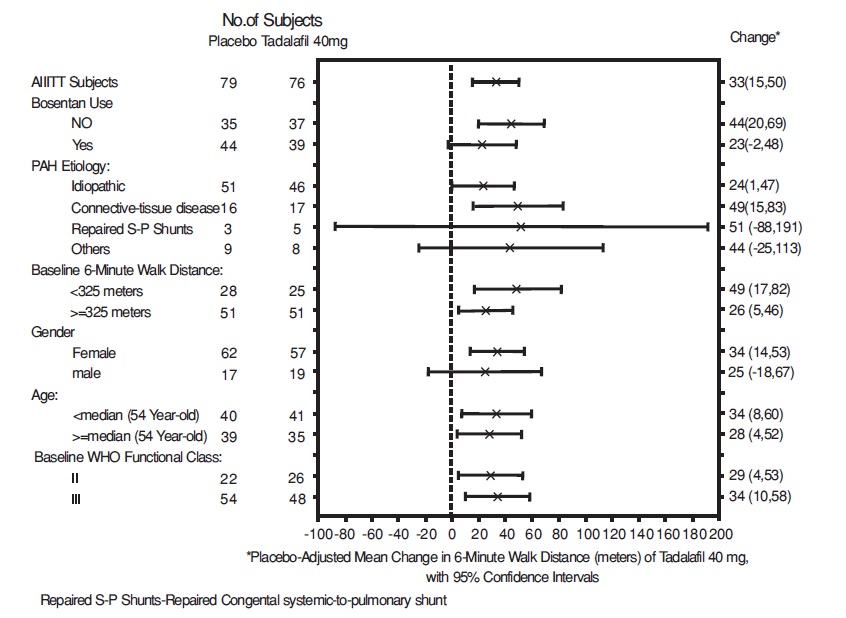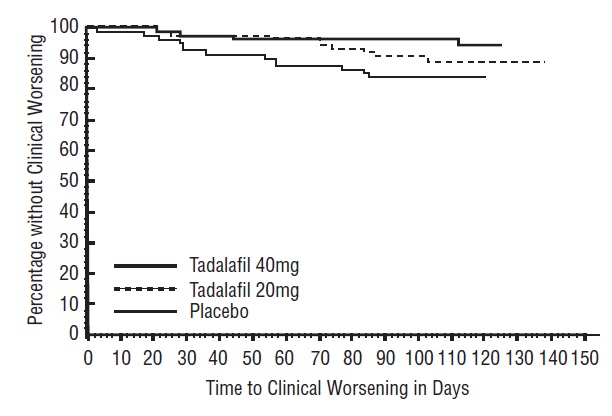 DRUG LABEL: TADLIQ
NDC: 46287-045 | Form: SUSPENSION
Manufacturer: CMP Pharma, Inc.
Category: prescription | Type: HUMAN PRESCRIPTION DRUG LABEL
Date: 20221015

ACTIVE INGREDIENTS: Tadalafil 20 mg/5 mL
INACTIVE INGREDIENTS: DIMETHICONE; SILICON DIOXIDE; CITRIC ACID MONOHYDRATE; GLYCERIN; POLYSORBATE 80; WATER; SODIUM BENZOATE; SUCRALOSE; TRISODIUM CITRATE DIHYDRATE; XANTHAN GUM

HIGHLIGHTS OF PRESCRIBING INFORMATION

These highlights do not include all the information needed to use TADLIQ safely and effectively. See full prescribing information for TADLIQ.
TADLIQ® (tadalafil) oral suspension
Initial U.S. Approval: 2003

1 INDICATIONS AND USAGE

TADLIQ is a phosphodiesterase 5 (PDE5) inhibitor indicated for the treatment of pulmonary arterial hypertension (PAH) (WHO Group 1) to improve exercise ability. Studies establishing effectiveness included predominately patients with NYHA Functional Class II – III symptoms and etiologies of idiopathic or heritable PAH (61%) or PAH associated with connective tissue diseases (23%). (1.1)

2 DOSAGE AND ADMINISTRATION

- 40 mg (10 mL) once daily, with or without food. (2.1)
- Use with ritonavir requires dosage adjustments. (2.4)

3 DOSAGE FORMS AND STRENGTHS

Oral Suspension: 20 mg/5 mL (3)

4 CONTRAINDICATIONS

- Concomitant organic nitrates (4.1)
- Concomitant Guanylate Cyclase (GC) Stimulators (4.2)
- History of known serious hypersensitivity reaction to TADLIQ, ADCIRCA® or CIALIS® (4.3)

5 WARNINGS AND PRECAUTIONS

- Hypotension: Carefully consider whether patients with certain underlying cardiovascular disease could be adversely affected by vasodilatory effects of TADLIQ. Not recommended in patients with pulmonary veno-occlusive disease. (5.1, 5.2)
- Effects on the eye: Sudden loss of vision could be a sign of non-arteritic ischemic optic neuropathy (NAION) and may be permanent. (5.3)
- Hearing impairment: Cases of sudden decrease or loss of hearing have been reported with tadalafil. (5.4)
- Concomitant PDE5 inhibitors: Avoid use with CIALIS, ADCIRCA or other PDE5 inhibitors. (5.5)
- Prolonged erection: Advise patients to seek emergency treatment if an erection lasts >4 hours. (5.6)

6 ADVERSE REACTIONS

The most common adverse reaction is headache. (6.1)

To report SUSPECTED ADVERSE REACTIONS, contact CMP Development, LLC at 1-844-321-1443, or FDA at 1-800-FDA-1088 or www.fda.gov/medwatch.

8 USE IN SPECIFIC POPULATIONS

Renal Impairment (2.2, 8.6, 12.3)

- Mild or moderate: Start with 20 mg once daily. (2.2, 8.6)
- Severe: Avoid use of TADLIQ. (2.2, 8.6)

Hepatic Impairment (2.2, 8.7, 12.3)

- Mild or moderate: Consider starting dose of 20 mg once daily. (2.3, 8.7)
- Severe: Avoid use of TADLIQ. (2.3, 8.7)

FULL PRESCRIBING INFORMATION

1 INDICATIONS AND USAGE

1.1 Pulmonary Arterial Hypertension

TADLIQ® is indicated for the treatment of pulmonary arterial hypertension (PAH) (WHO Group 1) to improve exercise ability. Studies establishing effectiveness included predominately patients with NYHA Functional Class II – III symptoms and etiologies of idiopathic or heritable PAH (61%) or PAH associated with connective tissue diseases (23%).

2 DOSAGE AND ADMINISTRATION

2.1 Pulmonary Arterial Hypertension

The recommended dose of TADLIQ is 40 mg (10 mL) taken once daily with or without food.

2.2 Dose Adjustment in Renal Impairment

Mild (creatinine clearance 51 to 80 mL/min) or moderate (creatinine clearance 31 to 50 mL/min): Start dosing at 20 mg (5mL) once daily. Increase to 40 mg (10 mL) once daily based on individual tolerability.

Severe (creatinine clearance <30 mL/min and on hemodialysis): Avoid use of TADLIQ because of increased tadalafil exposure (AUC), limited clinical experience, and the lack of ability to influence clearance by dialysis [see Use in Specific Populations (8.6)].

2.3 Dose Adjustment in Hepatic Impairment

Mild or moderate (Child Pugh Class A or B): Because of limited clinical experience in patients with mild to moderate hepatic cirrhosis, consider a starting dose of 20 mg (5 mL) once per day.

Severe (Child Pugh Class C): Patients with severe hepatic cirrhosis have not been studied. Avoid use of TADLIQ [see Use in Specific Populations (8.7)].

2.4 Dose Adjustment for Use with Ritonavir

Co-administration of TADLIQ in Patients on Ritonavir

In patients receiving ritonavir for at least one week, start TADLIQ at 20 mg (5 mL) once daily. Increase to 40 mg (10 mL) once daily based upon individual tolerability [see Drug Interactions (7.5) and Clinical Pharmacology (12.3)].

Co-administration of Ritonavir in Patients on TADLIQ

Avoid use of TADLIQ during the initiation of ritonavir. Stop TADLIQ at least 24 hours prior to starting ritonavir. After at least one week following the initiation of ritonavir, resume TADLIQ at 20 mg (5 mL) once daily. Increase to 40 mg (10 mL) once daily based upon individual tolerability [see Drug Interactions (7.5) and Clinical Pharmacology (12.3)].

3 DOSAGE FORMS AND STRENGTHS

Oral Suspension: 20 mg/5 mL; white to off-white opaque suspension with a peppermint flavor.

4 CONTRAINDICATIONS

4.1 Concomitant Organic Nitrates

TADLIQ is contraindicated in patients who are using any form of organic nitrate, either regularly or intermittently. Do not use nitrates within 48 hours of the last dose of TADLIQ. TADLIQ potentiates the hypotensive effect of nitrates. This potentiation is thought to result from the combined effects of nitrates and TADLIQ on the nitric oxide/cGMP pathway [see Clinical Pharmacology (12.2)].

4.2 Concomitant Guanylate Cyclase (GC) Stimulators

Coadministration of GC stimulators such as riociguat with TADLIQ is contraindicated. TADLIQ may potentiate the hypotensive effects of GC stimulators.

4.3 Hypersensitivity Reactions

TADLIQ is contraindicated in patients with a known serious hypersensitivity to tadalafil (TADLIQ, ADCIRCA® or CIALIS®). Hypersensitivity reactions have been reported, including Stevens-Johnson syndrome and exfoliative dermatitis [see Adverse Reactions (6.2)].

5 WARNINGS AND PRECAUTIONS

5.1 Hypotension

TADLIQ has vasodilatory properties that may result in transient decreases in blood pressure. Prior to prescribing TADLIQ, carefully consider whether patients with underlying cardiovascular disease could be affected adversely by such vasodilatory effects. Patients with preexisting hypotension, with autonomic dysfunction, with left ventricular outflow obstruction, may be particularly sensitive to the actions of vasodilators.

5.2 Worsening Pulmonary Vascular Occlusive Disease

Pulmonary vasodilators may significantly worsen the cardiovascular status of patients with pulmonary veno-occlusive disease (PVOD). Since there are no clinical data on administration of TADLIQ to patients with veno-occlusive disease, administration of TADLIQ to such patients is not recommended. Should signs of pulmonary edema occur when TADLIQ is administered, the possibility of associated PVOD should be considered.

5.3 Visual Loss

When used to treat erectile dysfunction, non-arteritic anterior ischemic optic neuropathy (NAION), a cause of decreased vision including permanent loss of vision, has been reported postmarketing in temporal association with the use of phosphodiesterase type 5 (PDE-5) inhibitors, including tadalafil. Most, but not all, of these patients had underlying anatomic or vascular risk factors for development of NAION, including but not necessarily limited to: low cup to disc ratio (“crowded disc”), age over 50, diabetes, hypertension, coronary artery disease, hyperlipidemia, and smoking. Based on published literature, the annual incidence of NAION is 2.5-11.8 cases per 100,000 in males aged ≥50 in the general population. An observational case-crossover study evaluated the risk of NAION when PDE5 inhibitor use, as a class, typical of erectile dysfunction treatment, occurred immediately before NAION onset (within 5 half-lives), compared to PDE5 inhibitor use in a prior time period. The results suggest an approximate doubling in the risk of NAION. Other risk factors for NAION, such as the presence of “crowded” optic disc, may have contributed to the occurrence of NAION in these studies.

Patients with known hereditary degenerative retinal disorders, including retinitis pigmentosa, were not included in the clinical trials, and use in these patients is not recommended.

5.4 Hearing Impairment

Cases of sudden decrease or loss of hearing, which may be accompanied by tinnitus and dizziness, have been reported in patients taking tadalafil. It is not possible to determine whether these events are related directly to the use of PDE5 inhibitors or to other factors [see Adverse Reactions (6.2)].

5.5 Combination with Other PDE5 Inhibitors

Tadalafil is also marketed for erectile dysfunction. The safety and efficacy of taking TADLIQ together with another PDE5 inhibitor has not been studied. Inform patients taking TADLIQ not to take other PDE5 inhibitors.

5.6 Prolonged Erection

There have been reports of prolonged erections greater than 4 hours and priapism (painful erections greater than 6 hours in duration) for this class of compounds. Patients with conditions that might predispose them to priapism (such as sickle cell anemia, multiple myeloma, or leukemia), or in patients with anatomical deformation of the penis (such as angulation, cavernosal fibrosis, or Peyronie's disease) are at an increased risk. Priapism, if not treated promptly, can result in irreversible damage to the erectile tissue. Patients who have an erection lasting greater than 4 hours, whether painful or not, should seek emergency medical attention.

6 ADVERSE REACTIONS

The following serious adverse reactions are discussed elsewhere in the labeling:

- Hypotension [see Warnings and Precautions (5.1)]
- Visual Loss [see Warnings and Precautions (5.3)]
- Hearing loss [see Warnings and Precautions (5.4)]
- Priapism [see Warnings and Precautions (5.6)]

6.1 Clinical Trials Experience

Because clinical trials are conducted under widely varying conditions, adverse reaction rates observed in the clinical trials of a drug cannot be directly compared to rates in the clinical trials of another drug and may not reflect the rates observed in practice.

Tadalafil was administered to 398 patients with PAH during clinical trials worldwide. In trials of tadalafil, a total of 311 and 251 subjects have been treated for at least 182 days and 360 days, respectively. The overall rates of discontinuation because of an adverse event (AE) in the placebo-controlled trial were 9% for tadalafil 40 mg and 15% for placebo. The rates of discontinuation because of AEs, other than those related to worsening of PAH, in patients treated with tadalafil 40 mg was 4% compared to 5% in placebo-treated patients.

In the placebo-controlled study, the most common AEs were generally transient and mild to moderate in intensity. Table 1 presents treatment-emergent adverse events reported by ≥9% of patients in the tadalafil 40 mg group and occurring more frequently than with placebo.

Table 1: Treatment-Emergent Adverse Events Reported by ≥9% of Patients in Tadalafil and More Frequent than Placebo by 2%
EVENT | Placebo (%) (N=82) | Tadalafil 20 mg (%) (N=82) | Tadalafil 40 mg (%) (N=79)
Headache | 15 | 32 | 42
Myalgia | 4 | 9 | 14
Nasopharyngitis | 7 | 2 | 13
Flushing | 2 | 6 | 13
Respiratory Tract Infection (Upper and Lower) | 6 | 7 | 13
Pain in Extremity | 2 | 5 | 11
Nausea | 6 | 10 | 11
Back Pain | 6 | 12 | 10
Dyspepsia | 2 | 13 | 10
Nasal Congestion (Including sinus congestion) | 1 | 0 | 9

6.2 Postmarketing Experience

The following adverse reactions have been identified during post-approval use of tadalafil. These events have been chosen for inclusion either because of their seriousness, reporting frequency, lack of clear alternative causation, or a combination of these factors. Because these reactions are reported voluntarily from a population of uncertain size, it is not always possible to estimate reliably their frequency or establish a causal relationship to drug exposure. The list does not include adverse events that are reported from clinical trials and that are listed elsewhere in this section.

Cardiovascular and cerebrovascular — Serious cardiovascular events, including myocardial infarction, sudden cardiac death, stroke, chest pain, palpitations, and tachycardia, have been reported postmarketing in temporal association with the use of tadalafil [see Contraindications (4.1)]. Most, but not all, of these patients had preexisting cardiovascular risk factors. Many of these events were reported to occur during or shortly after sexual activity, and a few were reported to occur shortly after the use of tadalafil without sexual activity. Others were reported to have occurred hours to days after the use of tadalafil and sexual activity. It is not possible to determine whether these events are related directly to tadalafil, to sexual activity, to the patient's underlying cardiovascular disease, to a combination of these factors, or to other factors.

Body as a whole — Hypersensitivity reactions including urticaria, Stevens–Johnson syndrome, and exfoliative dermatitis

Nervous — Migraine, seizure and seizure recurrence, and transient global amnesia

Ophthalmologic — Visual field defect, retinal vein occlusion, retinal artery occlusion, and NAION [see Warnings and Precautions (5.3)].

Otologic — Cases of sudden decrease or loss of hearing have been reported postmarketing in temporal association with the use of PDE5 inhibitors, including tadalafil. In some of the cases, medical conditions and other factors were reported that may have also played a role in the otologic adverse events. In many cases, medical follow-up information was limited. It is not possible to determine whether these reported events are related directly to the use of tadalafil, to the patient's underlying risk factors for hearing loss, a combination of these factors, or to other factors [see Warnings and Precautions (5.4)].

Urogenital — Priapism [see Warnings and Precautions (5.6)].

7 DRUG INTERACTIONS

7.1 Nitrates

Administration of nitrates within 48 hours after the last dose of TADLIQ is contraindicated [see Contraindications (4.1)].

7.2 Alpha-Blockers

PDE5 inhibitors, including TADLIQ, and alpha–adrenergic blocking agents are both vasodilators with blood-pressure-lowering effects. When vasodilators are used in combination, an additive effect on blood pressure may be anticipated. Clinical pharmacology studies have been conducted with coadministration of tadalafil with doxazosin, alfuzosin or tamsulosin [see Clinical Pharmacology (12.2)].

7.3 Antihypertensives

PDE5 inhibitors, including TADLIQ, are mild systemic vasodilators. Clinical pharmacology studies were conducted to assess the effect of tadalafil on the potentiation of the blood–pressure–lowering effects of selected antihypertensive medications (amlodipine, angiotensin II receptor blockers, bendroflumethiazide, enalapril, and metoprolol). Small reductions in blood pressure occurred following coadministration of tadalafil with these agents compared with placebo [see Clinical Pharmacology (12.2)].

7.4 Alcohol

Both alcohol and tadalafil, a PDE5 inhibitor, act as mild vasodilators. When mild vasodilators are taken in combination, blood pressure–lowering effects of each individual compound may be increased. Substantial consumption of alcohol (e.g., 5 units or greater) in combination with TADLIQ can increase the potential for orthostatic signs and symptoms, including increase in heart rate, decrease in standing blood pressure, dizziness, and headache. Tadalafil (10 mg or 20 mg) did not affect alcohol plasma concentrations and alcohol did not affect tadalafil plasma concentrations. [See Clinical Pharmacology (12.2)].

7.5 CYP3A Inhibitors/Inducers

Ritonavir

Ritonavir initially inhibits and later induces CYP3A, the enzyme involved in the metabolism of tadalafil. At steady state of ritonavir (about 1 week), the exposure to tadalafil is similar as in the absence of ritonavir [see Dosage and Administration (2.4) and Clinical Pharmacology (12.3)].

Potent Inhibitors of CYP3A

Tadalafil is metabolized predominantly by CYP3A in the liver. In patients taking potent inhibitors of CYP3A such as ketoconazole, and itraconazole, avoid use of TADLIQ [see Clinical Pharmacology (12.3)].

Potent Inducers of CYP3A

For patients chronically taking potent inducers of CYP3A, such as rifampin, avoid use of TADLIQ [see Clinical Pharmacology (12.3)].

8 USE IN SPECIFIC POPULATIONS

8.1 Pregnancy

Risk Summary

Pregnant women with untreated pulmonary arterial hypertension are at risk for adverse maternal and fetal outcomes (see Clinical Considerations). Available data from a randomized controlled trial, observational studies, and case series with tadalafil use in pregnant women have not identified a drug-associated risk of major birth defects, miscarriage or adverse maternal or fetal outcomes. In animal reproduction studies, no adverse developmental effects were observed with oral administration of tadalafil to pregnant rats or mice during organogenesis at exposures 7 times the exposure at the maximum recommended human dose (MRHD) of 40 mg/day based on AUC (see Data).

The estimated background risk of major birth defects and miscarriage for the indicated population is unknown. All pregnancies have a background risk of birth defect, loss, or other adverse outcomes. In the U.S. general population, the background risk of major birth defects and miscarriage in clinically recognized pregnancies is 2-4% and 15- 20%, respectively.

Clinical Considerations

Disease-Associated Maternal and/or Embryo/Fetal Risk

Pregnant women with untreated pulmonary arterial hypertension are at risk for heart failure, stroke, preterm delivery, and maternal and fetal death.

Data

Animal Data

Tadalafil and/or its metabolites cross the placenta, resulting in fetal exposure in rats.

Animal reproduction studies showed no evidence of teratogenicity, embryotoxicity, or fetotoxicity when tadalafil was given to pregnant rats or mice at unbound tadalafil exposures up to 7 times the exposure at the maximum recommended human dose (MRHD) of 40 mg/day during organogenesis based on AUC. In one of two perinatal/postnatal developmental studies in rats, a reduction of postnatal pup survival was observed at dose levels of 60, 200 and 1000 mg/kg. The no-observed-effect-level (NOEL) for developmental toxicity was 30 mg/kg, which provided maternal exposure to unbound tadalafil concentrations approximately 5 times the exposure at the MRHD based on AUC. Signs of maternal toxicity occurred at doses greater than 200 mg/kg/day, which produced AUCs greater than 8 times the exposure at the MRHD. Surviving offspring had normal development and reproductive performance.

8.2 Lactation

Risk Summary

There are no data on the presence of tadalafil and/or its metabolites in human milk, the effects on the breastfed child, or the effects on milk production. Tadalafil and/or its metabolites are present in the milk of lactating rats at concentrations approximately 2.4-times that found in the plasma. When a drug is present in animal milk, it is likely that the drug will be present in human milk.

The developmental and health benefits of breastfeeding should be considered along with the mother's clinical need for TADLIQ and any potential adverse effects on the breastfed child from TADLIQ or from the underlying maternal condition.

8.3 Females and Males of Reproductive Potential

Infertility

Males

Based on the data from 3 studies in adult males, tadalafil decreased sperm concentrations in the study of 10 mg tadalafil for 6 months and the study of 20 mg tadalafil for 9 months. This effect was not seen in the study of 20 mg tadalafil taken for 6 months. There was no adverse effect of tadalafil 10 mg or 20 mg on mean concentrations of testosterone, luteinizing hormone or follicle stimulating hormone. The clinical significance of the decreased sperm concentrations in the two studies is unknown. There have been no studies evaluating the effect of tadalafil on fertility in men or women [see Clinical Pharmacology (12.2)].

8.4 Pediatric Use

Safety and effectiveness of TADLIQ in pediatric patients have not been established.

8.5 Geriatric Use

Of the total number of subjects in the clinical study of tadalafil for pulmonary arterial hypertension, 28 percent were 65 and over, while 8 percent were 75 and over. No overall differences in safety were observed between subjects over 65 years of age compared to younger subjects or those over 75 years of age. No dose adjustment is warranted based on age alone; however, a greater sensitivity to medications in some older individuals should be considered. [See Clinical Pharmacology (12.3)].

8.6 Renal Impairment

For patients with mild or moderate renal impairment, start TADLIQ at 20 mg (5 mL) once daily. Increase the dose to 40 mg (10 mL) once daily based upon individual tolerability [see Dosage and Administration (2.2) and Clinical Pharmacology (12.3)].

In patients with severe renal impairment, avoid use of TADLIQ because of increased tadalafil exposure (AUC), limited clinical experience, and the lack of ability to influence clearance by dialysis [see Clinical Pharmacology (12.3)].

8.7 Hepatic Impairment

Because of limited clinical experience in patients with mild to moderate hepatic cirrhosis (Child-Pugh Class A or B), consider a starting dose of TADLIQ 20 mg (5 mL) once daily. Patients with severe hepatic cirrhosis (Child-Pugh Class C) have not been studied, thus avoid use of TADLIQ in such patients [see Dosage and Administration (2.3) and Clinical Pharmacology (12.3)].

10 OVERDOSAGE

Single doses up to 500 mg have been given to healthy male subjects, and multiple daily doses up to 100 mg have been given to male patients with erectile dysfunction. Adverse reactions were similar to those seen at lower doses. Doses greater than 40 mg have not been studied in patients with pulmonary arterial hypertension. In cases of overdose, standard supportive measures should be adopted as needed. Hemodialysis contributes negligibly to tadalafil elimination.

11 DESCRIPTION

TADLIQ contains tadalafil, a selective inhibitor of cyclic guanosine monophosphate (cGMP)–specific phosphodiesterase type 5 (PDE5). Tadalafil has the empirical formula C22H19N3O4 representing a molecular weight of 389.41. The structural formula is:

The chemical designation is pyrazino[1´,2´:1,6]pyrido[3,4–b]indole-1,4-dione, 6-(1,3-benzodioxol-5-yl)-2,3,6,7,12,12a-hexahydro-2-methyl-, (6R,12aR)-. It is a crystalline solid that is practically insoluble in water and very slightly soluble in ethanol.

TADLIQ oral suspension contains 20 mg/5 mL of tadalafil and the following inactive ingredients: 30% simethicone emulsion, citric acid monohydrate, glycerin, peppermint flavor, polysorbate 80, purified water, sodium benzoate, sucralose, trisodium citrate dihydrate, xanthan gum.

12 CLINICAL PHARMACOLOGY

12.1 Mechanism of Action

Tadalafil is an inhibitor of phosphodiesterase type 5 (PDE5), the enzyme responsible for the degradation of cyclic guanosine monophosphate (cGMP). Pulmonary arterial hypertension is associated with impaired release of nitric oxide by the vascular endothelium and consequent reduction of cGMP concentrations in the pulmonary vascular smooth muscle. PDE5 is the predominant phosphodiesterase in the pulmonary vasculature. Inhibition of PDE5 by tadalafil increases the concentrations of cGMP resulting in relaxation of pulmonary vascular smooth muscle cells and vasodilation of the pulmonary vascular bed.

Studies in vitro have demonstrated that tadalafil is a selective inhibitor of PDE5. PDE5 is found in pulmonary vascular smooth muscle, visceral smooth muscle, corpus cavernosum, skeletal muscle, platelets, kidney, lung, cerebellum, and pancreas.

In vitro studies have shown that the effect of tadalafil is more potent on PDE5 than on other phosphodiesterases. These studies have shown that tadalafil is >10,000 times as potent for PDE5 than for PDE1, PDE2, PDE4, and PDE7 enzymes, which are found in the heart, brain, blood vessels, liver, leukocytes, skeletal muscle, and other organs. Tadalafil is >10,000 times as potent for PDE5 than for PDE3, an enzyme found in the heart and blood vessels. Additionally, tadalafil is 700–fold as potent for PDE5 than for PDE6, which is found in the retina and is responsible for phototransduction. Tadalafil is >9,000-fold as potent for PDE5 than for PDE8, PDE9, and PDE10. Tadalafil is 14 times as potent for PDE5 than for PDE11A1 and 40 times as potent for PDE5 than for PDE11A4, two of the four known forms of PDE11. PDE11 is an enzyme found in human prostate, testes, skeletal muscle and in other tissues. In vitro, tadalafil inhibits human recombinant PDE11A1 and, to a lesser degree, PDE11A4 activities at concentrations within the therapeutic range. The physiological role and clinical consequence of PDE11 inhibition in humans have not been defined.

12.2 Pharmacodynamics

Effects on Blood Pressure When Administered with Nitrates

In clinical pharmacology studies, tadalafil (5 to 20 mg) was shown to potentiate the hypotensive effect of nitrates. Do not use TADLIQ in patients taking any form of nitrates [see Contraindications (4.1)].

A double–blind, placebo–controlled, crossover study in 150 male subjects at least 40 years of age (including subjects with diabetes mellitus and/or controlled hypertension) assessed the interaction between nitroglycerin and tadalafil. Subjects received daily doses of tadalafil 20 mg or matching placebo for 7 days and then were given a single dose of 0.4 mg sublingual nitroglycerin (NTG) at pre–specified timepoints following their last dose of tadalafil (2, 4, 8, 24, 48, 72, and 96 hours after tadalafil). A significant interaction between tadalafil and NTG was observed at each timepoint up to and including 24 hours. At 48 hours, by most hemodynamic measures, the interaction between tadalafil and NTG was not observed, although a few more tadalafil subjects compared to placebo experienced greater blood–pressure lowering effects at this timepoint. After 48 hours, the interaction was not detectable. [See Contraindications (4.1)].

Effects on Blood Pressure

The effects of tadalafil on blood pressure alone and administered with antihypertensives, alcohol, and alpha-blockers is shown in Figure 1.

a In some subjects, postural dizziness and orthostatic hypotension were observed. When tadalafil was administered with lower doses of alcohol (0.6 g/kg), hypotension was not observed, and dizziness occurred at a similar frequency to alcohol alone.

b In studies of tadalafil co-administration with doxazosin, the number of subjects with potentially clinically significant standing blood pressure decreases was greater for the combination. Some patients had symptoms associated with the decrease in blood pressure including syncope.

Figure 1: Effects of Tadalafil on Blood Pressure

Effects on Cardiac Electrophysiology

The effect of a single 100 mg dose of tadalafil (2.5 times the recommended dose) on the QT interval was evaluated at the time of peak tadalafil concentration in a randomized, double–blinded, placebo, and active–controlled (intravenous ibutilide) crossover study in 90 healthy males aged 18 to 53 years. The mean change in QTc (Fridericia QT correction) for tadalafil, relative to placebo, was 3.5 milliseconds (two–sided 90% CI=1.9, 5.1). The mean change in QTc (Individual QT correction) for tadalafil, relative to placebo, was 2.8 milliseconds (two–sided 90% CI=1.2, 4.4). In this study, the mean increase in heart rate associated with a 100 mg dose of tadalafil compared to placebo was 3.1 beats per minute.

Effects on Exercise Stress Testing

The effects of tadalafil on cardiac function, hemodynamics, and exercise tolerance were investigated in a single clinical pharmacology study. In this blinded crossover trial, 23 subjects with stable coronary artery disease and evidence of exercise–induced cardiac ischemia were enrolled. The primary endpoint was time to cardiac ischemia. The mean difference in total exercise time was 3 seconds (tadalafil 10 mg minus placebo), which represented no clinically meaningful difference. Further statistical analysis demonstrated that tadalafil was similar to placebo with respect to time to ischemia. Of note, in this study, in some subjects who received tadalafil followed by sublingual nitroglycerin in the post–exercise period, clinically significant reductions in blood pressure were observed, consistent with the augmentation by tadalafil of the blood–pressure–lowering effects of nitrates.

Effects on Vision

Single oral doses of PDE inhibitors have demonstrated transient dose-related impairment of color discrimination (blue/green), using the Farnsworth–Munsell 100–hue test, with peak effects near the time of peak plasma levels. This finding is consistent with the inhibition of PDE6, which is involved in phototransduction in the retina. In a study to assess the effects of a single dose of tadalafil 40 mg on vision (N=59), no effects were observed on visual acuity, intraocular pressure, or pupillometry. Across all clinical studies with tadalafil, reports of changes in color vision were rare (<0.1% of patients).

Effects on Sperm Characteristics

Three studies were conducted in men to assess the potential effect on sperm characteristics of tadalafil 10 mg (one 6-month study) and 20 mg (one 6-month and one 9-month study) administered daily. There were no adverse effects on sperm morphology or sperm motility in any of the three studies. In the study of 10 mg tadalafil for 6 months and the study of 20 mg tadalafil for 9 months, results showed a decrease in mean sperm concentrations relative to placebo, although these differences were not clinically meaningful. This effect was not seen in the study of 20 mg tadalafil taken for 6 months. In addition there was no adverse effect on mean concentrations of reproductive hormones, testosterone, luteinizing hormone or follicle stimulating hormone with either 10 or 20 mg of tadalafil compared to placebo.

Dose-Response Relationship

Dose-response relationships, between 20 mg and 40 mg, were not observed for 6-minute walk distance or pulmonary vascular resistance (PVR) in subjects with PAH in the placebo-controlled study. Median change from baseline in 6-minute walk distance was 32 meters and 35 meters at 16 weeks in subjects receiving 20 mg and 40 mg daily, respectively. Mean change from baseline PVR was -254 dynes*sec*cm^-5 and -209 dynes*sec*cm^-5 at 16 weeks in patients receiving 20 mg and 40 mg daily, respectively.

12.3 Pharmacokinetics

Over a dose range of 2.5 to 20 mg, tadalafil exposure (AUC) increases proportionally with dose in healthy subjects. In PAH patients administered between 20 and 40 mg of tadalafil, an approximately 50% greater AUC was observed indicating a less than proportional increase in exposure over the entire dose range of 2.5 to 40 mg. During tadalafil 20 and 40 mg once daily dosing, steady-state plasma concentrations were attained within 5 days, and exposure was approximately 30% higher than after a single dose.

Absorption — After single oral-dose administration, the maximum observed plasma concentration (Cmax) of tadalafil is achieved between 2 and 8 hours (median time of 4 hours). Absolute bioavailability of tadalafil following oral dosing has not been determined.

The rate and extent of absorption of tadalafil are not influenced by food; thus, TADLIQ may be taken with or without food.

Distribution — The mean apparent volume of distribution following oral administration is approximately 77 L, indicating that tadalafil is distributed into tissues. At therapeutic concentrations, 94% of tadalafil in plasma is bound to proteins.

Metabolism — Tadalafil is predominantly metabolized by CYP3A to a catechol metabolite. The catechol metabolite undergoes extensive methylation and glucuronidation to form the methylcatechol and methylcatechol glucuronide conjugate, respectively. The major circulating metabolite is the methylcatechol glucuronide. Methylcatechol concentrations are less than 10% of glucuronide concentrations. In vitro data suggests that metabolites are not expected to be pharmacologically active at observed metabolite concentrations.

Elimination — Following 40 mg, the mean oral clearance for tadalafil is 3.4 L/hr and the mean terminal half-life is 15 hours in healthy subjects. In patients with pulmonary hypertension not receiving concomitant bosentan, the mean oral clearance for tadalafil is 1.6 L/hr, and the mean terminal half-life is 35 hours. Tadalafil is excreted predominantly as metabolites, mainly in the feces (approximately 61% of the dose) and to a lesser extent in the urine (approximately 36% of the dose).

Population pharmacokinetics — In patients with pulmonary hypertension not receiving concomitant bosentan, the average tadalafil exposure at steady-state following 40 mg was 26% higher when compared to those of healthy volunteers. The results suggest a lower clearance of tadalafil in patients with pulmonary hypertension compared to healthy volunteers.

Geriatric patients

In healthy male elderly subjects (65 years or over) after a 10 mg dose, a lower oral clearance of tadalafil, resulting in 25% higher exposure (AUC) with no effect on Cmax was observed relative to that in healthy subjects 19 to 45 years of age.

Renal impairment

In clinical pharmacology studies using single-dose tadalafil (5 to 10 mg), tadalafil exposure (AUC) doubled in subjects with mild (creatinine clearance 51 to 80 mL/min) or moderate (creatinine clearance 31 to 50 mL/min) renal impairment. In subjects with end-stage renal disease on hemodialysis, there was a doubling in Cmax and AUC was 2.7- to 4.1 times as high following single-dose administration of 10 or 20 mg tadalafil, respectively. Exposure to total methylcatechol (unconjugated plus glucuronide) was 2- to 4 times as high in subjects with renal impairment, compared to those with normal renal function. Hemodialysis (performed between 24 and 30 hours post-dose) contributed negligibly to tadalafil or metabolite elimination [see Dosage and Administration (2.2)].

Hepatic impairment

In clinical pharmacology studies, tadalafil exposure (AUC) in subjects with mild or moderate hepatic impairment (Child-Pugh Class A or B) was comparable to exposure in healthy subjects when a dose of 10 mg was administered. There are no available data for doses higher than 10 mg of tadalafil in patients with hepatic impairment. Insufficient data are available for subjects with severe hepatic impairment (Child-Pugh Class C) [see Dosage and Administration (2.3)].

Patients with diabetes mellitus

In male patients with diabetes mellitus after a 10 mg tadalafil dose, exposure (AUC) was reduced approximately 19% and Cmax was 5% lower than that observed in healthy subjects. No dose adjustment is warranted.

Race

Pharmacokinetic studies have included subjects from different ethnic groups, and no differences in the typical exposure to tadalafil have been identified. No dose adjustment is warranted.

Gender

In healthy female and male subjects following single and multiple-doses of tadalafil, no clinically relevant differences in exposure (AUC and Cmax) were observed. No dose adjustment is warranted.

Drug interaction studies

Tadalafil is a substrate of and predominantly metabolized by CYP3A.

Cytochrome P450 3A4 inhibitors

Ketoconazole increased tadalafil exposure relative to the values for tadalafil alone (Figure 2). Although specific interactions have not been studied, other CYP3A inhibitors, such as erythromycin, itraconazole, and grapefruit juice, would likely increase tadalafil exposure.

Ritonavir

Ritonavir increased tadalafil 20–mg single-dose exposure relative to the values for tadalafil alone. Ritonavir inhibits and induces CYP3A, the enzyme involved in the metabolism of tadalafil, in a time-dependent manner. The initial inhibitory effect of ritonavir on CYP3A may be mitigated by a more slowly evolving induction effect so that after about 1 week of ritonavir twice daily, the exposure of tadalafil is similar in the presence of and absence of ritonavir [see Dosage and Administration (2.4) and Drug Interactions (7.5)]. Although specific interactions have not been studied, other HIV protease inhibitors would likely increase tadalafil exposure.

Cytochrome P450 3A4 inducers

Rifampin (600 mg daily), a CYP3A inducer, reduced tadalafil 10 mg single–dose exposure (AUC) by 88% and Cmax by 46%, relative to the values for tadalafil 10 mg alone [see Drug Interactions (7.5)].

Bosentan, a substrate of CYP2C9 and CYP3A and a moderate inducer of CYP3A, CYP2C9 and possibly CYP2C19, reduced tadalafil systemic exposure following multiple-dose co-administration (Figure 2). Although specific interactions have not been studied, other CYP3A inducers, such as carbamazepine, phenytoin, and phenobarbital, would likely decrease tadalafil exposure.

Exposure changes of tadalafil following co-administration with other drugs are shown in Figure 2.

a Ritonavir is also a CYP2C9/CYP2C19/CYP2D6 Inhibitor and CYP3A inducer.

b [see Dosage and Administration (2.4)].

c Bosentan is also a CYP2C9/CYP2C19 inducer.

Figure 2: Impact of Other Drugs on the Pharmacokinetics of Tadalafil

Cytochrome P450 substrates

Tadalafil is not expected to cause clinically significant inhibition or induction of the clearance of drugs metabolized by cytochrome P450 (CYP) isoforms.

Exposure changes of drugs following co-administration with tadalafil are shown in Figure 3.

a A small augmentation (increase of 3 beats per minute) in heart rate was observed with theophylline.

b Tadalafil (40 mg qd) had no clinically significant effect on exposure (AUC and Cmax) of bosentan metabolites.

c 95% CI

Figure 3: Impact of Tadalafil on the Pharmacokinetics of Other Drugs

13 NONCLINICAL TOXICOLOGY

13.1 Carcinogenesis, Mutagenesis, Impairment of Fertility

Carcinogenesis — Tadalafil was not carcinogenic to rats or mice when administered daily for 2 years at doses up to 400 mg/kg/day. Systemic drug exposures, as measured by AUC of unbound tadalafil, were approximately 5–fold for mice, and 7– and 14–fold for male and female rats, respectively, the exposures at the maximum recommended human dose (MRHD) of 40 mg.

Mutagenesis — Tadalafil was not mutagenic in the in vitro bacterial Ames assays or the forward mutation test in mouse lymphoma cells. Tadalafil was not clastogenic in the in vitro chromosomal aberration test in human lymphocytes or the in vivo rat micronucleus assays.

Impairment of Fertility — There were no effects on fertility, reproductive performance or reproductive organ morphology in male or female rats given oral doses of tadalafil up to 400 mg/kg/day, a dose producing AUCs for unbound tadalafil of 6–fold for males or 17–fold for females the exposures at the MRHD of 40 mg. In beagle dogs given tadalafil daily for 3 to 12 months, there was treatment–related non–reversible degeneration and atrophy of the seminiferous tubular epithelium in the testes in 20–100% of the dogs that resulted in a decrease in spermatogenesis in 40–75% of the dogs at doses of ≥10 mg/kg/day. Systemic exposure (based on AUC) at no–observed–adverse-effect–level (NOAEL) (10 mg/kg/day) for unbound tadalafil was similar to that expected in humans at the MRHD of 40 mg.

There were no treatment–related testicular findings in rats or mice treated with doses up to 400 mg/kg/day for 2 years.

13.2 Animal Toxicology and/or Pharmacology

Animal studies showed vascular inflammation in tadalafil–treated mice, rats, and dogs. In mice and rats, lymphoid necrosis and hemorrhage were seen in the spleen, thymus, and mesenteric lymph nodes at unbound tadalafil exposure of 1– to 17–fold the human exposure (AUCs) at the MRHD of 40 mg. In dogs, an increased incidence of disseminated arteritis was observed in 1– and 6-month studies at unbound tadalafil exposure of 0.5– to 38–fold the human exposure (AUC) at the MRHD of 40 mg. In a 12–month dog study, no disseminated arteritis was observed, but 2 dogs exhibited marked decreases in white blood cells (neutrophils) and moderate decreases in platelets with inflammatory signs at unbound tadalafil exposures of approximately 4– to 10–fold the human exposure at the MRHD of 40 mg. The abnormal blood–cell findings were reversible within 2 weeks upon removal of the drug.

14 CLINICAL STUDIES

14.1 Tadalafil for Pulmonary Arterial Hypertension

A randomized, double-blind, 16 week placebo-controlled study was conducted in 405 patients with pulmonary arterial hypertension, defined as a resting mean pulmonary artery pressure (mPAP) ≥25 mm Hg, pulmonary capillary wedge pressure (PCWP) ≤15 mm Hg, and pulmonary vascular resistance (PVR) ≥3 Wood units via right heart catheterization. Allowed background therapy included bosentan (maintenance dosing up to 125 mg twice daily) and chronic anticoagulation. The use of prostacyclin or analogue, L–arginine, phosphodiesterase inhibitor, or other chronic PAH medications were not permitted.

Subjects were randomly assigned to 1 of 5 treatment groups (tadalafil 2.5, 10, 20, 40 mg, or placebo) in a 1:1:1:1:1 ratio. Subjects had to be at least 12 years of age and had a diagnosis of PAH that was idiopathic, heritable, related to connective tissue disease, anorexigen use, human immunodeficiency virus (HIV) infection, associated with an atrial-septal defect, or associated with surgical repair of a congenital systemic-to-pulmonary shunt of least 1 year in duration (for example, ventricular septal defect, patent ductus arteriosus). Patients with a history of left-sided heart disease, severe renal insufficiency, or pulmonary hypertension related to conditions other than specified in the inclusion criteria were not eligible for enrollment.

The mean age of all subjects was 54 years (range 14 - 90 years) with the majority of subjects being Caucasian (81%) and female (78%). PAH etiologies were predominantly idiopathic or heritable PAH (61%) and related to connective tissue disease (23%). More than half (53%) of the subjects in the study were receiving concomitant bosentan therapy. The majority of subjects had a World Health Organization (WHO) Functional Class III (65%) or II (32%). The mean baseline 6-minute walk distance (6-MWD) was 343 meters. Of the 405 subjects, 341 completed the study.

The primary efficacy endpoint was the change from baseline at week 16 in 6-MWD (see Figure 4). In the tadalafil 40 mg treatment group, the placebo-adjusted mean change increase in 6-MWD was 33 meters (95% C.I. 15-50 meters; p=0.0004). The improvement in 6-MWD was apparent at 8 weeks of treatment and then maintained at week 12 and week 16.

Figure 4: 6-Minute Walk Distance (meters) Mean Change from Baseline, with 95% Confidence Intervals

Placebo-adjusted changes in 6-MWD at 16 weeks were evaluated in subgroups (see Figure 5). In patients taking only 40 mg tadalafil (i.e., without concomitant bosentan), the placebo-adjusted mean change in 6-MWD was 44 meters. In patients taking 40 mg of tadalafil and concomitant bosentan therapy, the placebo adjusted mean change in 6-MWD was 23 meters.

Figure 5: Placebo-adjusted Mean Change in 6-Minute Walk Distance (meters) of Tadalafil 40 mg, with 95% Confidence Intervals

There was less clinical worsening (defined as death, lung transplantation, atrial septostomy, hospitalization because of worsening PAH, initiation of new PAH therapy [prostacyclin or analog, endothelin receptor antagonist, PDE5 inhibitor], or worsening WHO functional class) in the Tadalafil 40 mg group compared to the placebo group and the groups that used lower doses of tadalafil.

Table 2: Number (percent) with Clinical Worseninga
 |  | Tadalafil
 | Placebo N=82 | 2.5 mg N=82 | 10 mg N=80 | 20 mg N=82 | 40 mg N=79
Total with clinical worsening | 13 (16) | 10 (12) | 7 (9) | 8 (10) | 4 (5)
Death | 1 | 0 | 1 | 0 | 0
Hospitalization for worsening PAH | 2 | 2 | 3 | 0 | 1
New PAH therapy | 0 | 1 | 0 | 2 | 1
Worsening WHO class | 11 | 10 | 6 | 6 | 3
a Subjects may be counted in more than one category

The Kaplan-Meier plot of times to clinical worsening is shown below in Figure 6.

Figure 6: Kaplan-Meier Plot of Time to Clinical Worsening

14.2 Long-Term Treatment of Pulmonary Arterial Hypertension

Patients (N=357) from the placebo-controlled study entered a long-term extension study. Of these, 311 patients have been treated with tadalafil for at least 6 months and 182 for 1 year (median exposure 356 days; range 2 days to 415 days). The survival rate in the extension study was 96.5 per 100 patient years. Without a control group, these data must be interpreted cautiously.

16 HOW SUPPLIED/STORAGE AND HANDLING

16.1 How Supplied

TADLIQ (tadalafil) Oral Suspension, 20 mg/5 mL is a white to off-white, opaque, peppermint-flavored suspension. It is available in a 150 mL bottle (NDC 46287-045-15).

16.2 Storage

Store at 20°C to 25°C (68°F to 77°F): excursions permitted to 15°C to 30°C (59°F to 86°F) [see USP Controlled Room Temperature]. Shake well for 30 seconds before use. Dispense in a tight container as defined in the USP.

Keep out of reach of children.

17 PATIENT COUNSELING INFORMATION

Advise patient to read the FDA-Approved patient labeling (Patient Information)

- Inform patients that tadalafil is also marketed as CIALIS for erectile dysfunction (ED) and for the signs and symptoms of benign prostatic hyperplasia (BPH). Advise patients taking TADLIQ not to take CIALIS or other PDE5 inhibitors.
- Advise patients to seek immediate medical attention in the event of a sudden loss of vision in one or both eyes while taking TADLIQ. Such an event may be a sign of NAION. Also discuss with patients that there is an increased risk of NAION in individuals who have already experienced NAION in one eye, including whether such individuals could be adversely affected by use of vasodilators such as PDE5 inhibitors.
- Advise patients to seek prompt medical attention in the event of sudden decrease or loss of hearing while taking TADLIQ. These events may be accompanied by tinnitus and dizziness.

Distributed by:
CMP Pharma, Inc.
Farmville, NC 27828

3067 Rev 1022

PATIENT INFORMATION

TADLIQ® (Tad-leek)

(tadalafil) oral suspension

What is the most important information I should know about TADLIQ?

Never take TADLIQ with any nitrate or guanylate cyclase stimulator medicines:

- Your blood pressure could drop quickly to an unsafe level.
- You could get dizzy, faint and even have a heart attack or stroke.

Nitrates include:

- Medicines that treat chest pain (angina)
- Nitroglycerin in any form including tablets, patches, sprays, and ointments
- Other nitrate medicines (isosorbide mononitrate or dinitrate)
- Street drugs that are inhaled, called “poppers” (amyl nitrate, butyl nitrate or nitrite)

Guanylate cyclase stimulators include:

- Riociguat, a medicine that treats pulmonary arterial hypertension and chronic thromboembolic pulmonary hypertension

Ask your healthcare provider or pharmacist if you are not sure if you take a nitrate or guanylate cyclase stimulator medicine.

See “What are the possible side effects of TADLIQ?” for more information about side effects.

What is TADLIQ?

TADLIQ is a prescription medicine used to treat pulmonary arterial hypertension (PAH) to improve your ability to exercise. PAH is a type of high blood pressure in the arteries of your lungs.

It is not known if TADLIQ is safe or effective in children.

Do not take TADLIQ if you:

- take any medicines called nitrates
- use recreational drugs called “poppers” like amyl nitrate, butyl nitrate or nitrite
- take any medicines called guanylate cyclase stimulators
- are allergic to tadalafil (TADLIQ or the medicines ADCIRCA or CIALIS) or any other ingredient in TADLIQ. See the end of this leaflet for a complete list of ingredients in TADLIQ.

Before you take TADLIQ, tell your healthcare provider about all of your medical conditions, including if you:

- have low blood pressure
- have pulmonary veno-occlusive disease (PVOD)
- have heart problems
- have liver problems
- have kidney problems or get dialysis
- have retinitis pigmentosa, a rare genetic eye disease
- have ever had any sudden vision loss, including an eye problem called non-arteritic anterior ischemic optic neuropathy (NAION).
- have ever had hearing problems such as ringing in the ears, dizziness, or loss of hearing
- have a deformed penis shape or Peyronie's disease
- have blood cell problems such as sickle cell anemia, multiple myeloma, or leukemia
- are pregnant or plan to become pregnant. It is not known if TADLIQ will harm your unborn baby.
- are breastfeeding or plan to breastfeed. It is not known if TADLIQ passes into your breast milk. Talk with your healthcare provider about the best way to feed your baby.

Tell your healthcare provider about all the medicines you take, including prescription and over-the counter medicines, vitamins, and herbal supplements. TADLIQ and other medicines may affect each other.

Especially tell your healthcare provider if you take:

- nitrates or guanylate cyclase stimulators (see “What is the most important information I should know about TADLIQ?”)
- medicines for erectile dysfunction (impotence). TADLIQ contains tadalafil, which is the same medicine found in another medicine called CIALIS. CIALIS is used for the treatment of male erectile dysfunction and for the signs and symptoms of benign prostatic hyperplasia. Do not take CIALIS or other medicines for erectile dysfunction, or other PDE5 inhibitors during treatment with TADLIQ.

Ask your healthcare provider or pharmacist for a list of these medicines, if you are not sure.

Know the medicines you take. Keep a list of them and show it to your healthcare provider and pharmacist when you get a new medicine.

How should I take TADLIQ?

- Take TADLIQ exactly as your healthcare provider tells you.
- Take TADLIQ 1 time each day.
- Shake the TADLIQ bottle well for 30 seconds before measuring your dose.
- TADLIQ can be taken with or without food.
- Your healthcare provider may change your dose.
- Do not change your dose or stop taking TADLIQ without speaking to your healthcare provider.
- If you take too much TADLIQ, call your healthcare provider or go to the nearest hospital emergency room right away.

What should I avoid while taking TADLIQ?

Do not have more than 5 alcohol-containing drinks in a short period of time during treatment with TADLIQ. Drinking too much alcohol can increase your chances of low blood pressure, increased heart rate, dizziness and headache.

What are the possible side effects of TADLIQ?

TADLIQ may cause serious side effects, including:

- See “What is the most important information I should know about TADLIQ?”
- Decreased blood pressure. TADLIQ may cause low blood pressure that last for a short time.
- Decreased eyesight or permanent loss of vision in one or both eyes could be a sign of non-arteritic anterior ischemic optic neuropathy (NAION). There is an increased risk of NAION in people who have already experienced NAION in one eye. If you notice a sudden decrease or loss of vision in one or both eyes, contact your healthcare provider right away.
- Sudden decrease or loss of hearing, sometimes with ringing in the ears and dizziness. If you notice a sudden decrease or loss of hearing, contact your healthcare provider right away.
- In men, an erection that lasts more than 4 hours (with or without pain). Talk to your healthcare provider or get emergency medical help right away. An erection that lasts more than 4 hours must be treated as soon as possible or you can have lasting damage to your penis, including the inability to have erections.

The most common side effects of TADLIQ is headache.

These are not all of the possible side effects of TADLIQ.

Call your doctor for medical advice about side effects. You may report side effects to FDA at 1-800-FDA-1088.

How should I store TADLIQ?

- Store TADLIQ at room temperature between 68°F to 77°F (20°C to 25°C).

Keep TADLIQ and all medicines out of the reach of children.

General information about the safe and effective use of TADLIQ.

Medicines are sometimes prescribed for purposes other than those listed in a Patient Information leaflet. Do not use TADLIQ for a condition for which it was not prescribed. Do not give TADLIQ to other people, even if they have the same symptoms that you have. It may harm them. You can ask your healthcare provider or pharmacist for information about TADLIQ that is written for healthcare professionals.

What are the ingredients in TADLIQ?

Active Ingredient: tadalafil

Inactive Ingredients: 30% simethicone emulsion, citric acid monohydrate, glycerin, peppermint flavor, polysorbate 80, purified water, sodium benzoate, sucralose, tri-sodium citrate dihydrate, xanthan gum.

Distributed by: CMP Pharma, Inc., 8026 US Highway 264A, Farmville, NC 27828
For more information, go to www.TADLIQ.com or call 1-844-321-1443

This Patient Information has been approved by the U.S. Food and Drug Administration.

Issued: 10/2022

PACKAGE LABEL – Tadliq 20 mg/5 mL

150 mL

Rx only

NDC 46287-045-15

tadliq®

(Tadalafil) Oral Suspension

20 mg/5 mL

FOR ORAL USE ONLY.

SHAKE WELL FOR 30 SECONDS BEFORE USE.